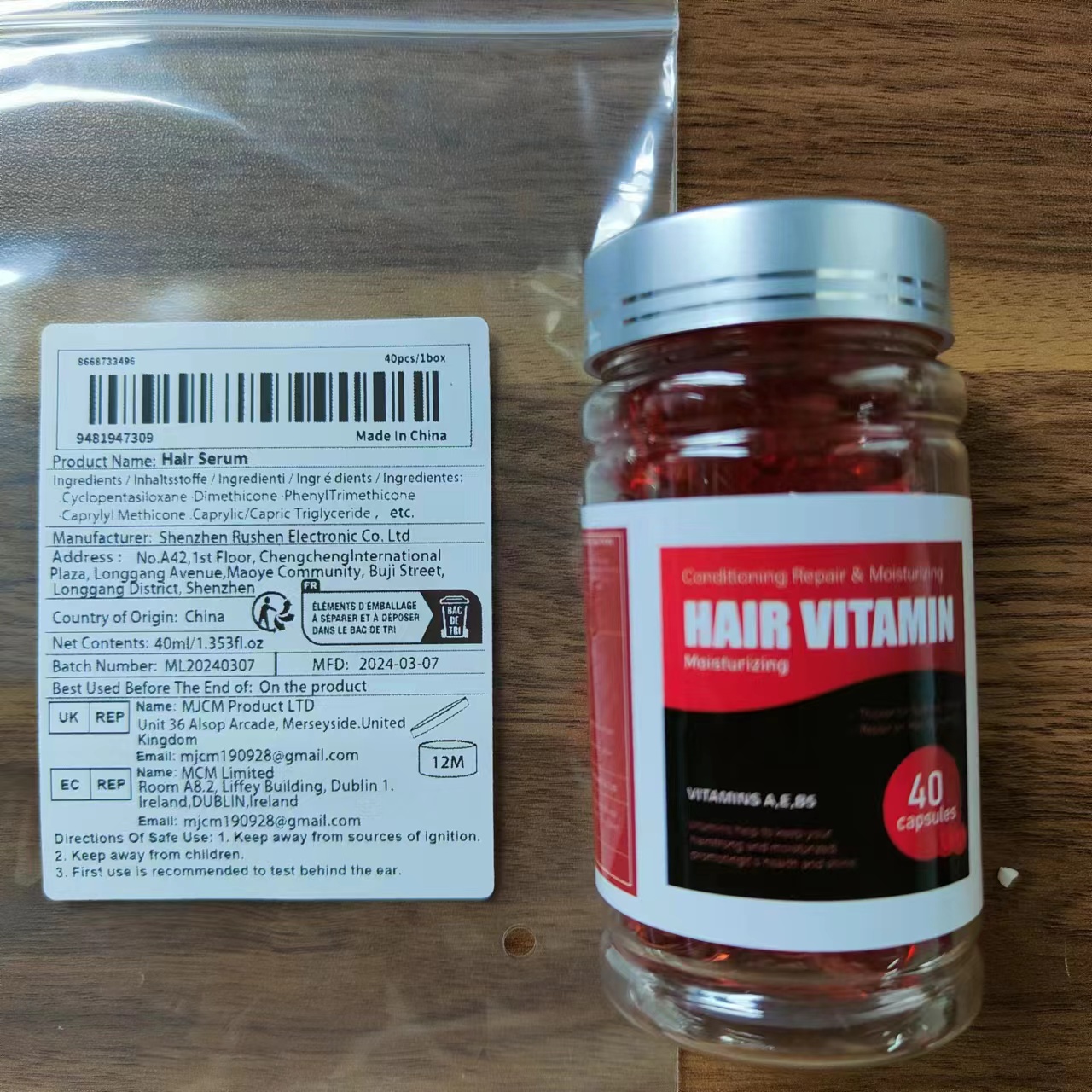 DRUG LABEL: Halr Serum
NDC: 84431-002 | Form: OIL
Manufacturer: Hair Serum
Category: otc | Type: HUMAN OTC DRUG LABEL
Date: 20240704

ACTIVE INGREDIENTS: DIMETHICONE 6 mg/1 g; PENTAMETHYL CYCLOPENTASILOXANE 6 mg/1 g
INACTIVE INGREDIENTS: PHENYL TRIMETHICONE; CAPRYLIC/CAPRIC/LAURIC TRIGLYCERIDE

ACTIVE INGREDIENT

Cyclopentasiloxane 6mg

Dimethicone 6mg

PURPOSE

Anti-dandruff, de-greasing, improves scalp health

ues

It makes the hair softer and more beautiful.

WARNINGS

For exteral use only

Do not use on damaged or broken skin.

When using this product
Only for external use. do not ingest.
Avoid direct contact with eyes.

Stop use and ask a doctor if
rash occurs

Keep out of reach of children.
if swallowed, get medical help or contact a Poison Control Center right away.

Ask Doctor
When Pregnant or breast-feeding.

DOSAGE AND ADMINISTRATION

1.CUT THE TOP OF THE CAPSULE

2.POUR THE SERUM INTO YOUR PALM

3.USE ON DRY, CLEAN HAIR

4.LET IT DRY, DO NOT RINSEOFF. STYLE AS USUAL

STORAGE AND HANDLING

Before use, read all information on thecarton Store at controlled room temperature20 to 25 C (68 to 77°F)

INACTIVE INGREDIENT

PHENYL TRIMETHICONE
CAPRYLIC/CAPRIC/LAURIC TRIGLYCERIDE